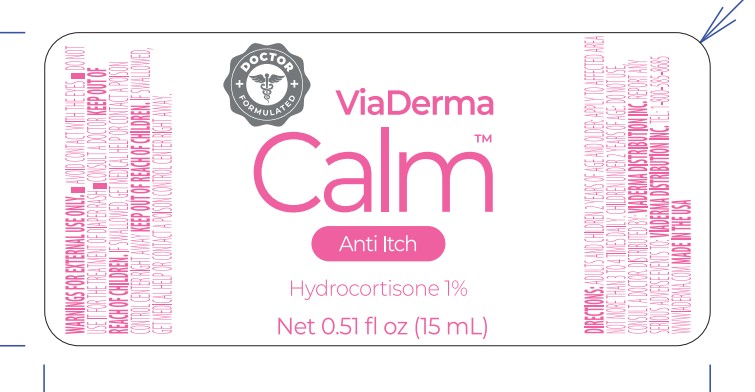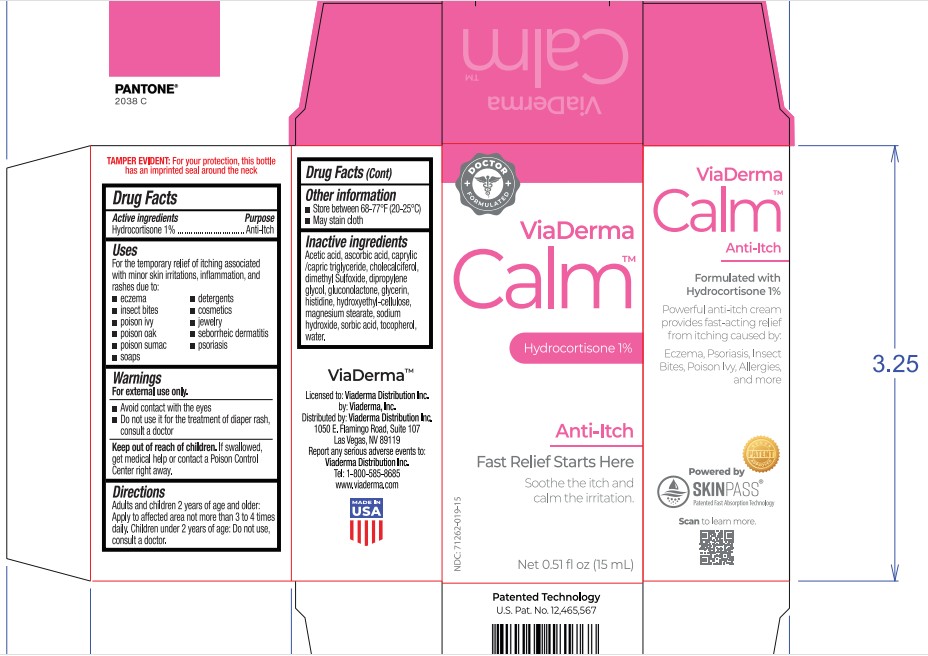 DRUG LABEL: Viaderma Calm Anti-Itch
NDC: 71262-019 | Form: SOLUTION
Manufacturer: VIADERMA DISTRIBUTION INC
Category: otc | Type: HUMAN OTC DRUG LABEL
Date: 20260127

ACTIVE INGREDIENTS: HYDROCORTISONE 10 mg/1 mL
INACTIVE INGREDIENTS: ACETIC ACID; MEDIUM-CHAIN TRIGLYCERIDES; CHOLECALCIFEROL; DIMETHYL SULFOXIDE; DIPROPYLENE GLYCOL; GLUCONOLACTONE; GLYCERIN; HISTIDINE; HYDROXYETHYL CELLULOSE, UNSPECIFIED; MAGNESIUM STEARATE; SODIUM HYDROXIDE; SORBIC ACID; STEARIC ACID; TETRAHEXYLDECYL ASCORBATE; TOCOPHEROL; WATER

Viaderma Calm Anti-Itch

Active ingredient

Hydrocortisone 1%

Purpose

Anti Itch

Uses

For the temporary relief of itching associated with minor skin irritations, inflammation, and rashes due to:

• eczema • detergents
• insect bites • cosmetics
• poison ivy • jewelry
• poison oak • seborrheic dermatitis
• poison sumac • psoriasis
• soaps

Warnings

For external use only.

• Avoid contact with the eyes
• Do not use it for the treatment of diaper rash, consult a doctor

Keep out of reach of children.

If swallowed, get medical help or contact a Poison Control Center right away.

Directions

Adults and children 2 years of age and older: Apply to affected area not more than 3 to 4 times daily. Children under 2 years of age: Do not use, consult a doctor.

Other information

- Store between 68-77°F (20-25°C)
- May stain cloth

Inactive ingredients

Acetic acid, caprylic/capric triglyceride, cholecalciferol, dimethyl sulfoxide, dipropylene glycol, gluconolactone, glycerin, histidine, hydroxyethyl-cellulose, magnesium stearate, sodium hydroxide, sorbic acid, stearic acid, tetrahexyldecyl ascorbate, tocopherol, water.